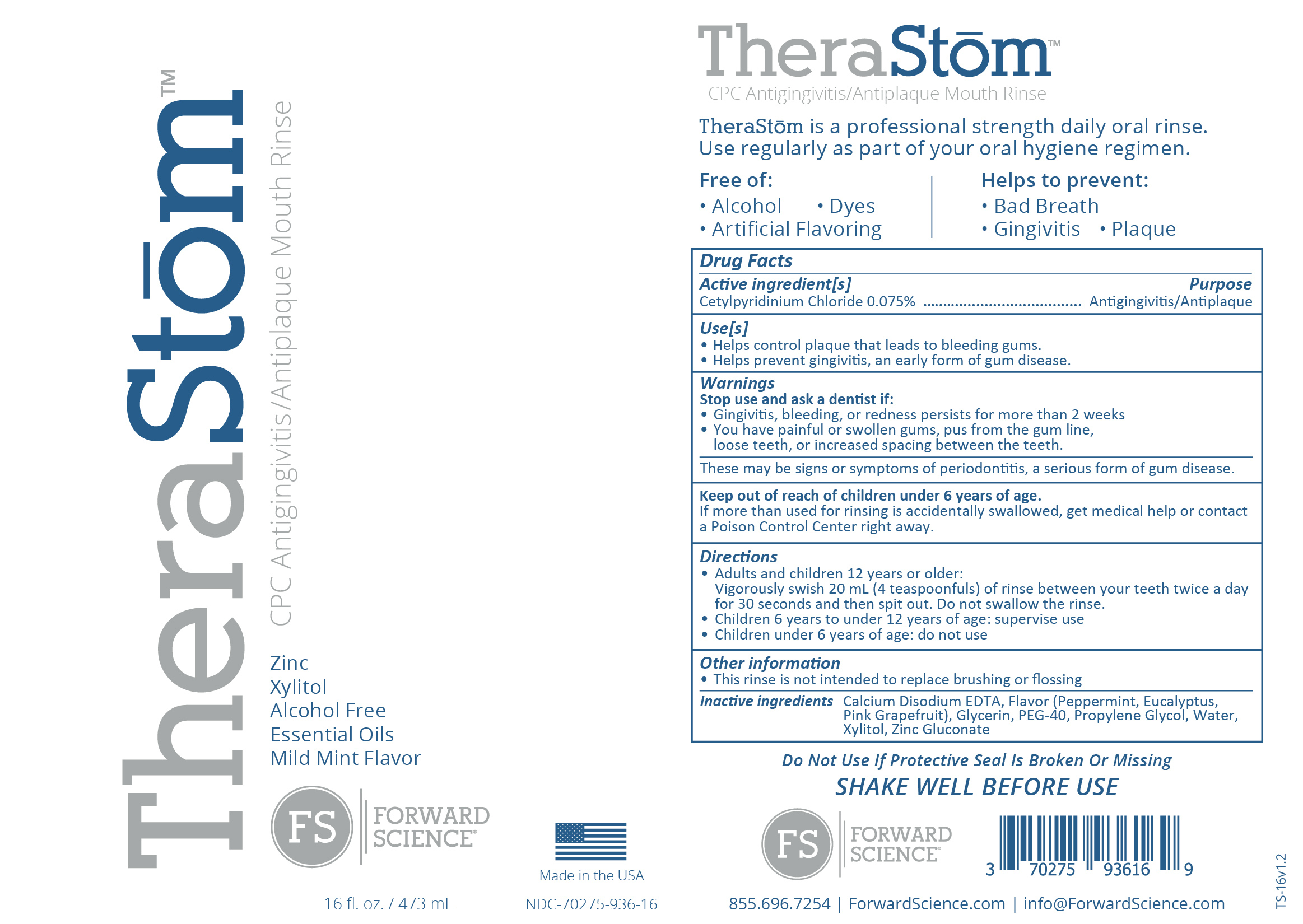 DRUG LABEL: TheraStom
NDC: 70275-936 | Form: RINSE
Manufacturer: Forward Science Technologies LLC
Category: otc | Type: HUMAN OTC DRUG LABEL
Date: 20251226

ACTIVE INGREDIENTS: CETYLPYRIDINIUM CHLORIDE 0.075 mg/0.1 mL
INACTIVE INGREDIENTS: PROPYLENE GLYCOL; EUCALYPTUS OIL; POLYOXYL 40 HYDROGENATED CASTOR OIL; WATER; EDETATE CALCIUM DISODIUM; GLYCERIN; GRAPEFRUIT OIL; XYLITOL; ZINC GLUCONATE; PEPPERMINT OIL

TheraStom

Inactive Ingredients

Calcium Disodium EDTA, Flavor (Peppermint, Eucalyptus, Pink Grapefruit), Glycerin, PEG-40, Propylene Glycol, Water, Xylitol, Zinc Gluconate

Active Ingredient

Cetylpyridinium Chloride 0.075%

Purpose

Antigingivitis/Antiplaque

Use(s)

• Helps control plaque that leads to bleeding gums.
• Helps prevent gingivitis, an early form of gum disease .

Warnings

Stop use and ask a dentist if:
• Gingivitis, bleeding, or redness persists for more than 2 weeks
• You have painful or swollen gums, pus from the gum line, loose teeth, or increased spacing between the teeth.
These may be signs or symptoms of periodontitis, a serious form of gum disease.

Keep out of reach of children under 6 years of age.
If more than used for rinsing is accidentally swallowed, get medical help or contact a Poison Control Center right away.

Directions

• Adults and children 12 years or older: Vigorously swish 20 ml (4 teaspoonfuls) of rinse between your teeth twice a day for 30 seconds and then spit out. Do not swallow the rinse.
• Children 6 years to under 12 years of age: supervise use
• Children under 6 years of age: do not use

Other information

This rinse is not intended to replace brushing or flossing

Dosage

Vigorously swish 20 ml (4 teaspoonfuls) of rinse between your teeth twice a day for 30 seconds and then spit out.